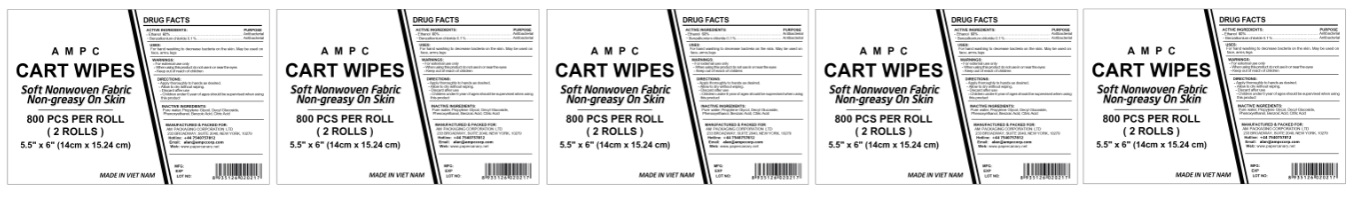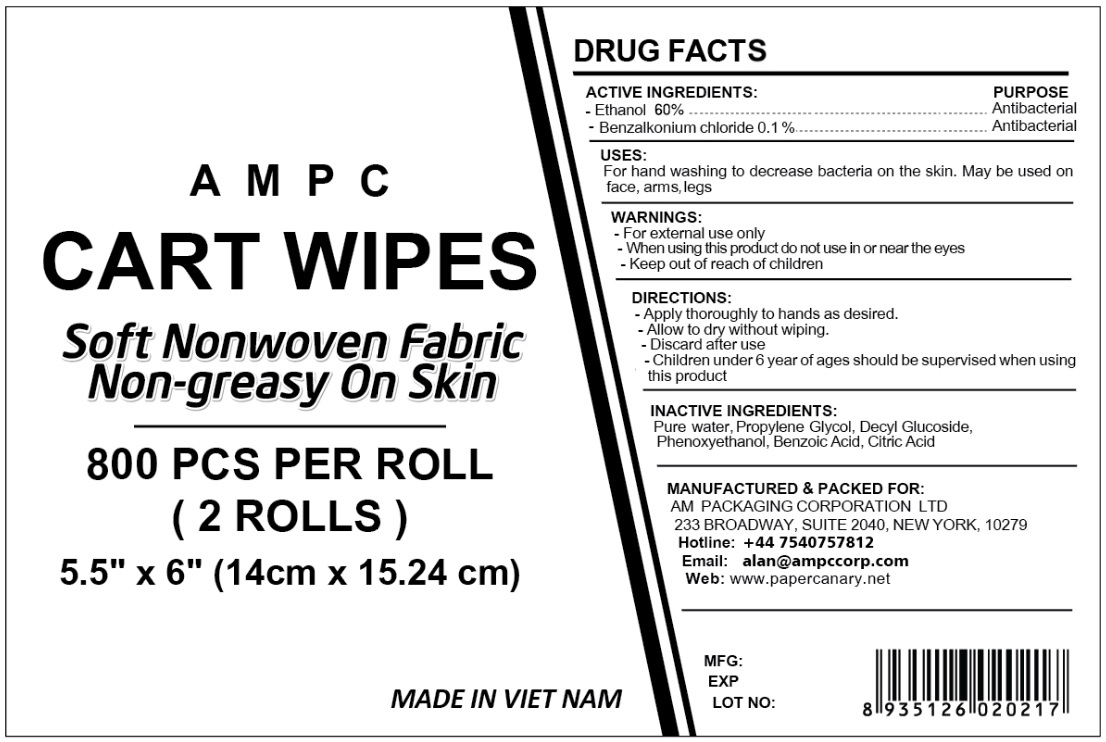 DRUG LABEL: ANTIBACTERIAL WIPES
NDC: 79854-100 | Form: CLOTH
Manufacturer: TISSUE PAPER PRODUCTION & TRADING CO.,LTD
Category: otc | Type: HUMAN OTC DRUG LABEL
Date: 20200813

ACTIVE INGREDIENTS: ALCOHOL 60 mL/100 g; BENZALKONIUM CHLORIDE 0.1 g/100 g
INACTIVE INGREDIENTS: WATER; PROPYLENE GLYCOL; DECYL GLUCOSIDE; PHENOXYETHANOL; BENZOIC ACID; CITRIC ACID MONOHYDRATE

AMPC CART WIPES

ACTIVE INGREDIENTS:

-Ethanol 60%

-Benzalkonium chloride 0.1%

PURPOSE

Antibacterial

Antibacterial

USES:

For hands washing to decrease bacteria on the skin. May be used on face, arms, legs

WARNINGS:

-For external use only

-When using this product do not use in or near the eyes

-Keep out of reach of children

DIRECTIONS:

-Apply thoroughly to hands as desired.

-Allow to dry without wiping.

-Discard after use

-Children under 6 years of age should be supervised when using this product

INACTIVE INGREDIENTS:

Pure water, Propylene Glycol, Decyl Glucoside, Phenoxyethanol, Benzoic Acid, Citric Acid

Soft Nonwoven Fabric

Non-greasy On Skin

MADE IN VIETNAM

MANUFACTURED & PACKED FOR:

AM PACKAGING CORPORATION LTD

233 BROADWAY, SUITE 2040, NEW YORK, 10279

Hotline: +44 7540757812

Email: alan@ampccorp.com

Web: www.papercanary.net

MFG:

EXP

LOT NO: